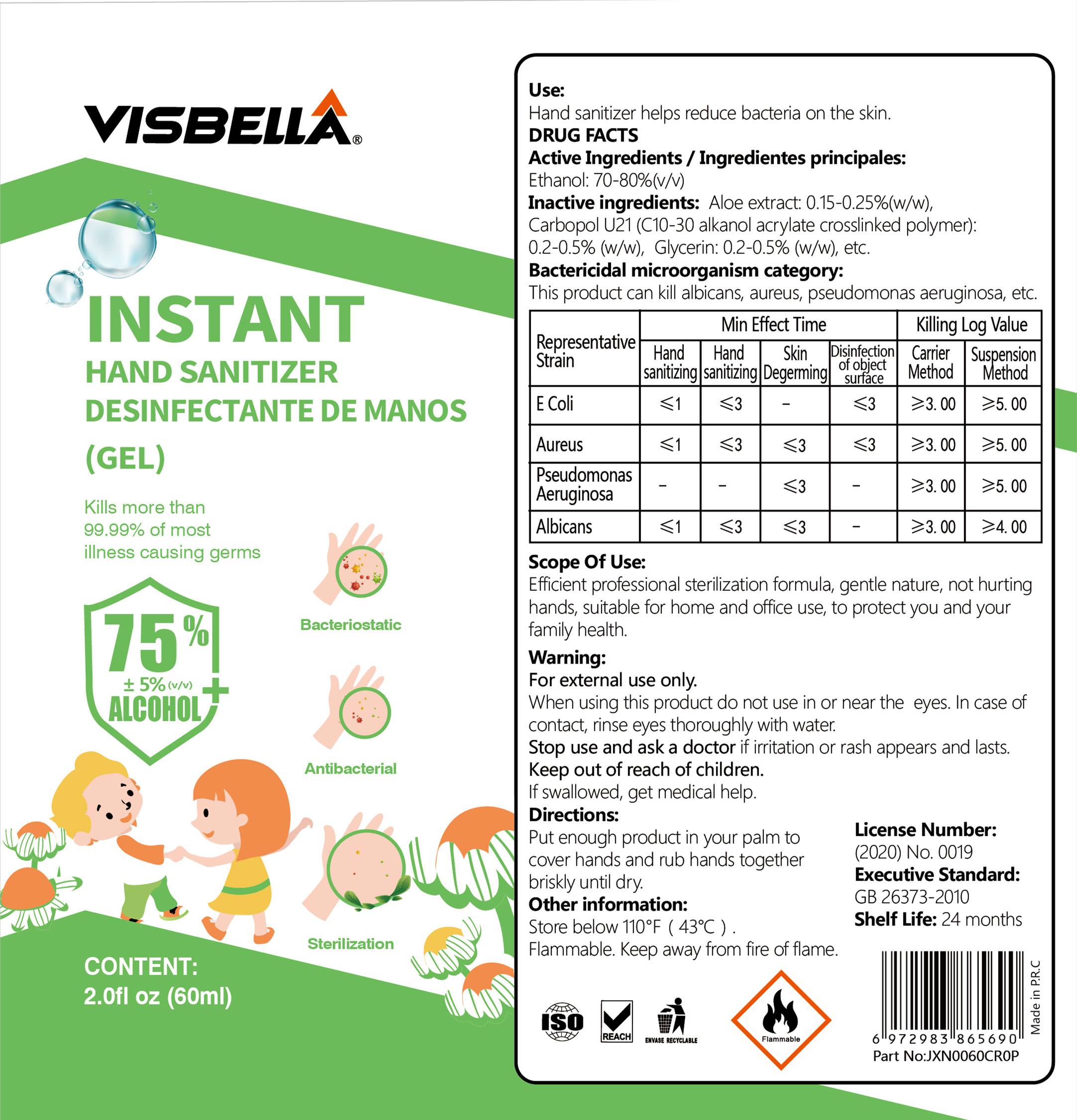 DRUG LABEL: Instant Hand Sanitizer(Gel)
NDC: 40760-006 | Form: GEL
Manufacturer: Huzhou Guoneng New Material Co., Ltd.
Category: otc | Type: HUMAN OTC DRUG LABEL
Date: 20200708

ACTIVE INGREDIENTS: ALCOHOL 45 mL/60 mL
INACTIVE INGREDIENTS: GLYCERIN; ALOE

PURPOSE

Disinfection
Sterilization
No Rinseing

ACTIVE INGREDIENT

alcohol

keep out of reach of children

INDICATIONS AND USAGE

Put enough product in your palm tocover hands and rub hands together briskly until dry.

When using this product do not use in or near the eyes. In case of contact, rinse eyes thoroughly with water.Stop use and ask a doctor if iritation or rash appears and lasts.

DOSAGE AND ADMINISTRATION

Store below 110°F (43°C).Flammable. Keep away from fire of flame.

INACTIVE INGREDIENT

aloe extract

glycerin